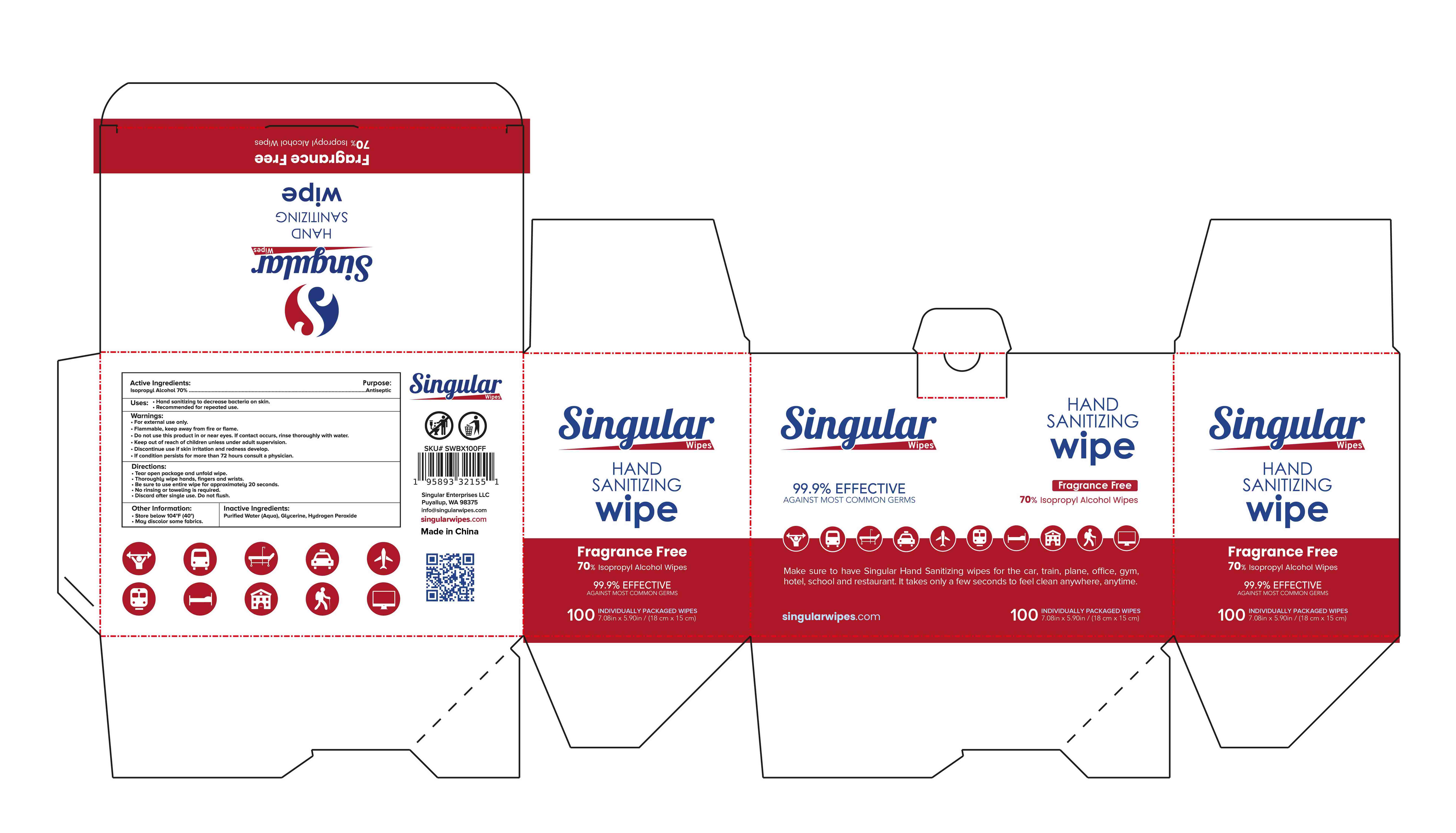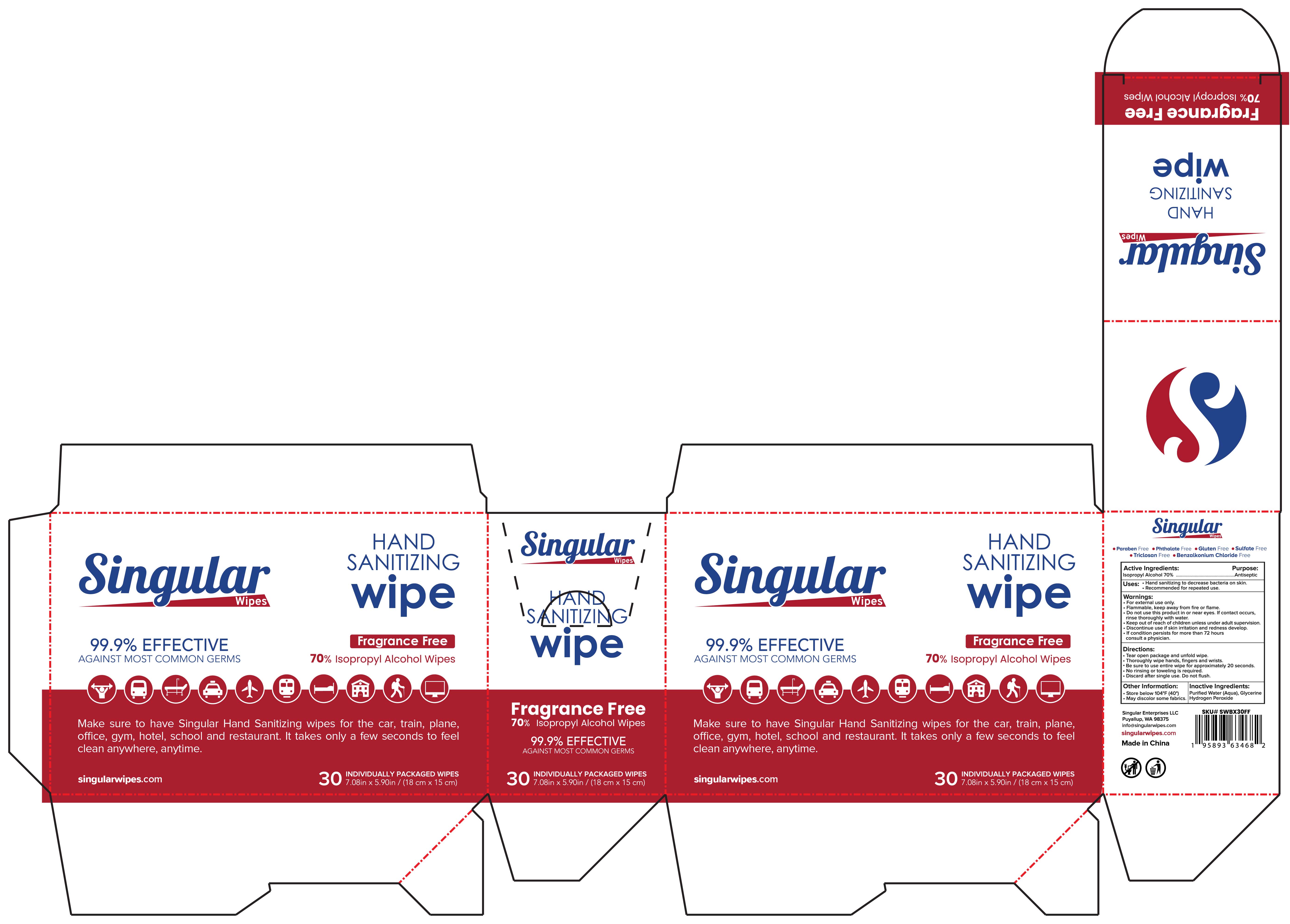 DRUG LABEL: Hand Sanitizer Wipes
NDC: 54860-494 | Form: CLOTH
Manufacturer: Shenzhen Lantern Scicence Co.,Ltd.
Category: otc | Type: HUMAN OTC DRUG LABEL
Date: 20250812

ACTIVE INGREDIENTS: ISOPROPYL ALCOHOL 70 mL/100 1
INACTIVE INGREDIENTS: HYDROGEN PEROXIDE; GLYCERIN; WATER

Hand Sanitizer Wipes

Active Ingredient

lsopropyl Alcohol 70%.........Antiseptic

Uses

Hand sanitizing to decrease bacteria on skin.
Recommended for repeated use.

Warning

For external use only.
Flammable, keep away from fire or flame.
Do not use this product in or near eyes. lf contact occursrinse thoroughly with water.

Keep out of reach of children unless under adult supervision.

Discontinue use if skin irritation and redness develop.

If condition persists for more than 72 hoursconsult a physician.

Directions

Tear open package and unfold wipe.
Thoroughly wipe hands, fingers and wrists.
Be sure to use entire wipe for approximately 20 seconds.

No rinsing or toweling is required.

Discard after single use. Do not flush.

Keep out of reach of children unless under adult supervision..Discontinue use if skin irritation and redness develop.

other Information

Store below 104°F(40°)
May discolor some fabrics

Inactive ingredients

Purified Water (Aqua), Glycerine.Hydrogen Peroxide.

packing